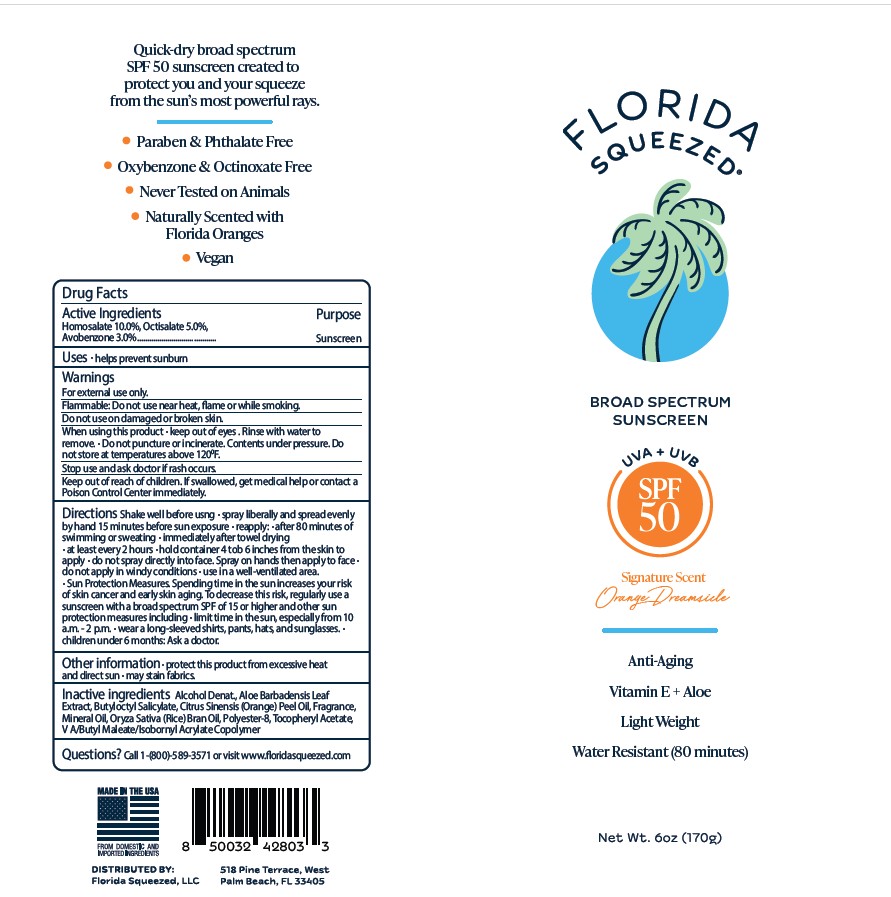 DRUG LABEL: Broad Spectrum SPF 50 sunscreen
NDC: 83810-012 | Form: SPRAY
Manufacturer: Florida Squeezed
Category: otc | Type: HUMAN OTC DRUG LABEL
Date: 20250826

ACTIVE INGREDIENTS: AVOBENZONE 3 g/100 g; HOMOSALATE 15 g/100 g; OCTISALATE 10 g/100 g
INACTIVE INGREDIENTS: ALCOHOL; ALOE; BUTYLOCTYL SALICYLATE; ORANGE OIL; FRAGRANCE 13576; MINERAL OIL; ORYZA SATIVA (RICE) BRAN; POLYESTER-8 (1400 MW, CYANODIPHENYLPROPENOYL CAPPED); .ALPHA.-TOCOPHEROL ACETATE

SPF 50 (Avobenzone 3.0%, Homosalate 10.0%, Octisalate 5.0%)

Uses

· helps prevent sunburn

Warnings For external use only.

Flammable:Do not use near heat, flame or while smoking.
Do not useon damaged or broken skin.
When using this product· keep out of eyes . Rinse with water to
remove. · Do not puncture or incinerate. Contents under pressure. Do
not store at temperatures above 1200F.
Stop use and ask doctor ifrash occurs.

Keep out of reach of children.

If swallowed, get medical help or contact a Poison Control Center immediately.

Directions

Shake well before usng · spray liberally and spread evenly by hand 15 minutes before sun exposure · reapply: · after 80
minutes of swimming or sweating · immediately after towel drying · at least every 2 hours · hold container 4 tob 6 inches from the skin to
apply · do not spray directly into face. Spray on hands then apply to face · do not apply in windy conditions · use in a well-ventilated area.
· Sun Protection Measures.Spending time in the sun increases your risk of skin cancer and early skin aging. To decrease this risk, regularly
use a sunscreen with a broad spectrum SPF of 15 or higher and other sun protection measures including · limit time in the sun, especially
from 10 a.m. - 2 p.m. · wear a long-sleeved shirts, pants, hats, and sunglasses. · children under 6 months: Ask a doctor.

Other information ·

protect this product from excessive heat and direct sun · may stain fabrics.

Inactive ingredients

Alcohol, ALOE, BUTYLOCTYL SALICYLATE, ORANGE OIL, FRAGRANCE, MINERAL OIL, ORYZA SATIVA (RICE) BRAN, POLYESTER-8, tocopheryl acetate